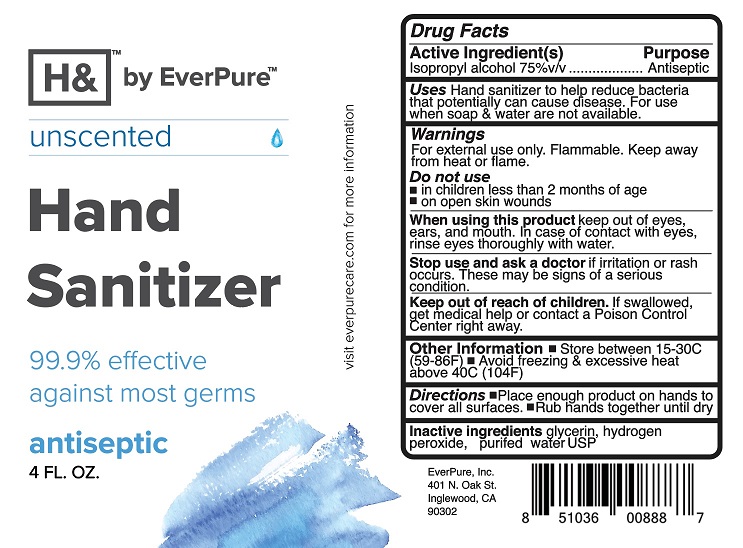 DRUG LABEL: Hand Sanitizer
NDC: 72655-001 | Form: LIQUID
Manufacturer: Everbrands, Inc. dba EverPure, Inc.
Category: otc | Type: HUMAN OTC DRUG LABEL
Date: 20201208

ACTIVE INGREDIENTS: ISOPROPYL ALCOHOL 75 mL/100 mL
INACTIVE INGREDIENTS: GLYCERIN; HYDROGEN PEROXIDE; WATER

Hand Sanitizer

Drug Facts

Active ingredients

Isopropyl Alcohol 75%

Purpose

Antiseptic

INDICATIONS AND USAGE

Uses Hand sanitizer to help reduce bacteria
that potentially can cause disease. For use
when soap & water are not available.

Warnings
For external use only. Flammable. Keep away
from heat or flame.

Do not use
• in children less than 2 months of age
• on open skin wounds

When using this product keep out of eyes,
ears, and mouth. In case of contact with eyes,
rinse eyes thoroughly with water.

Stop use and ask a doctor if irritation or rash
occurs. These may be signs of a serious condition.

Keep out of reach of children. If swallowed,
get medical help or contact a Poison Control
Center right away.

Other Information • Store between 15-30C
(59-86F) • Avoid freezing & excessive heat
above 40C (104F)

DOSAGE AND ADMINISTRATION

Directions •Place enough product on hands to
cover all surfaces. •Rub hands together until dry

Inactive ingredients glycerin, hydrogen
peroxide, purifed water USP

Product Label

H&™ by EverPure™

unscented

Hand

Sanitizer

99.9% effective

against most germs

antiseptic

4 FL. OZ.

visit everpurecare.com for more information

EverPure, Inc.
401 N. Oak St.
Inglewood, CA
90302

8 51036 00888 7